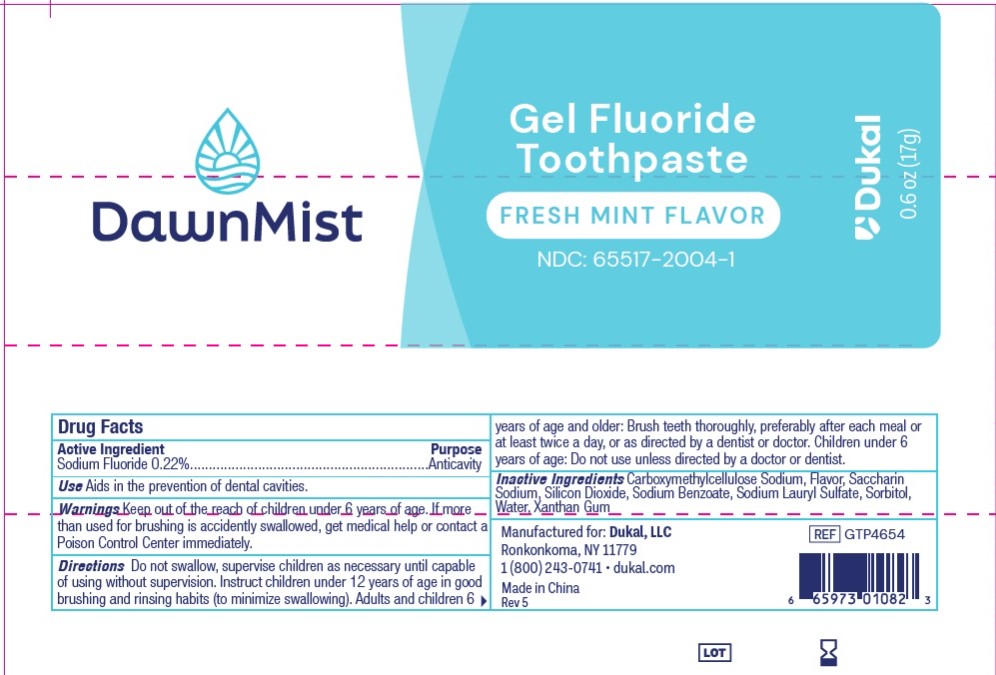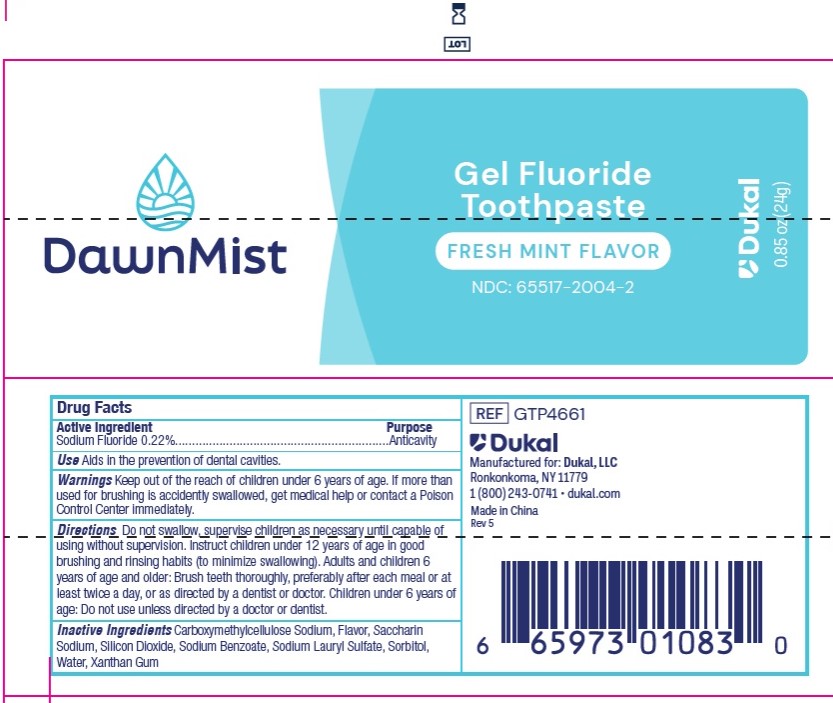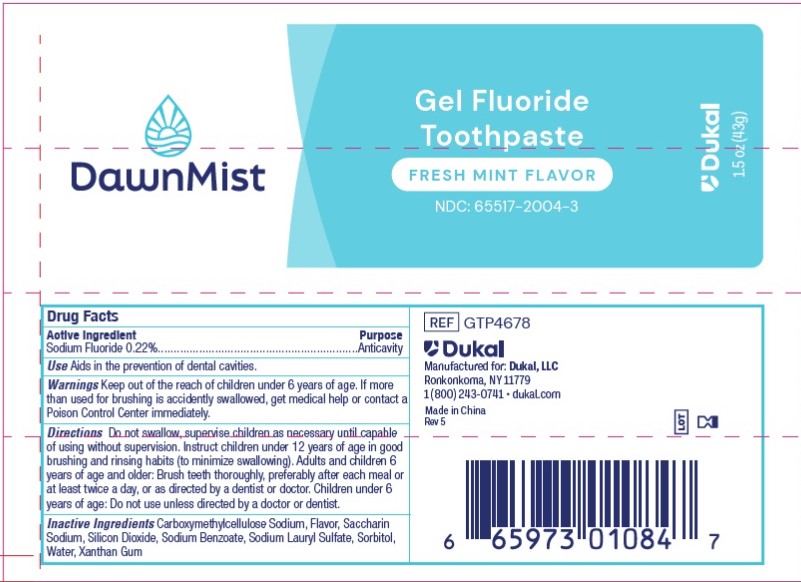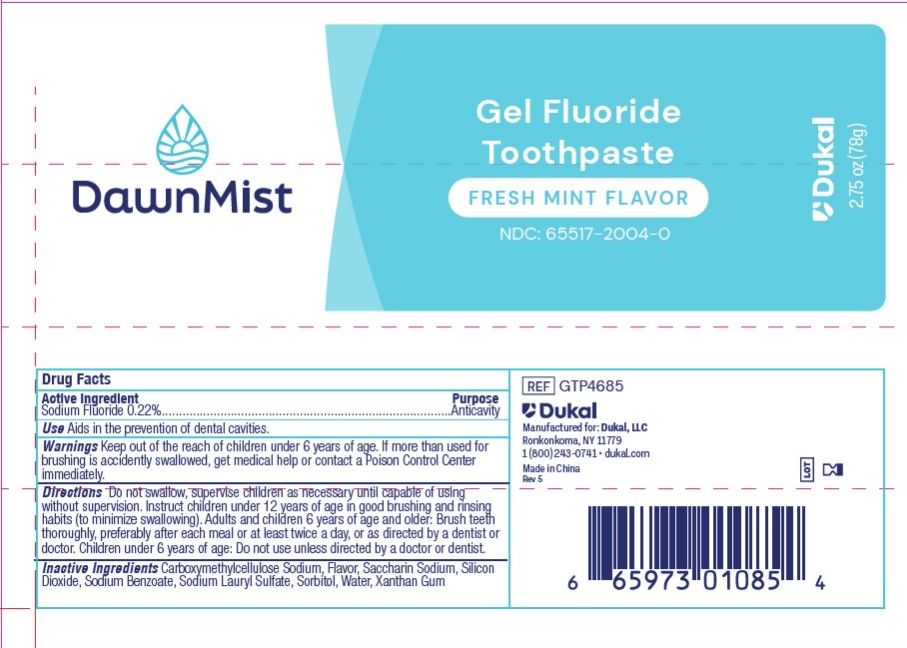 DRUG LABEL: DawnMist Gel Fluoride
NDC: 65517-2004 | Form: GEL, DENTIFRICE
Manufacturer: Dukal LLC
Category: otc | Type: HUMAN OTC DRUG LABEL
Date: 20250207

ACTIVE INGREDIENTS: SODIUM FLUORIDE 0.22 g/100 g
INACTIVE INGREDIENTS: XANTHAN GUM; CARBOXYMETHYLCELLULOSE SODIUM; SILICON DIOXIDE; SODIUM LAURYL SULFATE; WATER; SACCHARIN SODIUM; SODIUM BENZOATE; SORBITOL

65517-2004 - DawnMist Gel Fluoride Toothpaste

ACTIVE INGREDIENT

Sodium Fluoride 0.22%

PURPOSE

Anticavity

INDICATIONS AND USAGE

Aids in the prevention of dental cavities.

WARNINGS

Keep out of the reach of children under 6 years of age.

KEEP OUT OF REACH OF CHILDREN

Keep out of the reach of children under 6 years of age. If more than used for brushing is accidently swallowed, get medical help or contact a Poison Control Center immediately.

DOSAGE AND ADMINISTRATION

Do not swallow, supervise children as necessary until capable of using without supervision. Instruct Children under 12 years of age in good brushing and rinsing habits (to minimize swallowing). Adults and children 6 years of age and older: Brush teeth thoroughly, preferably after each meal or at least twice a day, or as directed by a dentist or doctor. Children under 6 years of age: Do not use unless directed by a doctor or dentist.

INACTIVE INGREDIENT

Carboxymethylcellulose Sodium, Flavor, Saccharin Sodium, Silicon Dioxide, Sodium Benzoate, Sodium Lauryl Sulfate, Sorbitol, Water, Xanthan Gum

PACKAGE LABEL

DawnMist

Gel Fluoride Toothpaste

FRESH MINT FLAVOR

NDC: 65517-2004-1

Dukal

0.6oz (17g)

PACKAGE LABEL

DawnMist

Gel Fluoride Toothpaste

FRESH MINT FLAVOR

NDC: 65517-2004-2

Dukal

0.85oz (24g)

PACKAGE LABEL

DawnMist

Gel Fluoride Toothpaste

FRESH MINT FLAVOR

NDC: 65517-2004-3

Dukal

1.5oz (43g)

PACKAGE LABEL

DawnMist

Gel Fluoride Toothpaste

FRESH MINT FLAVOR

NDC: 65517-2004-0

Dukal

2.75oz (78g)